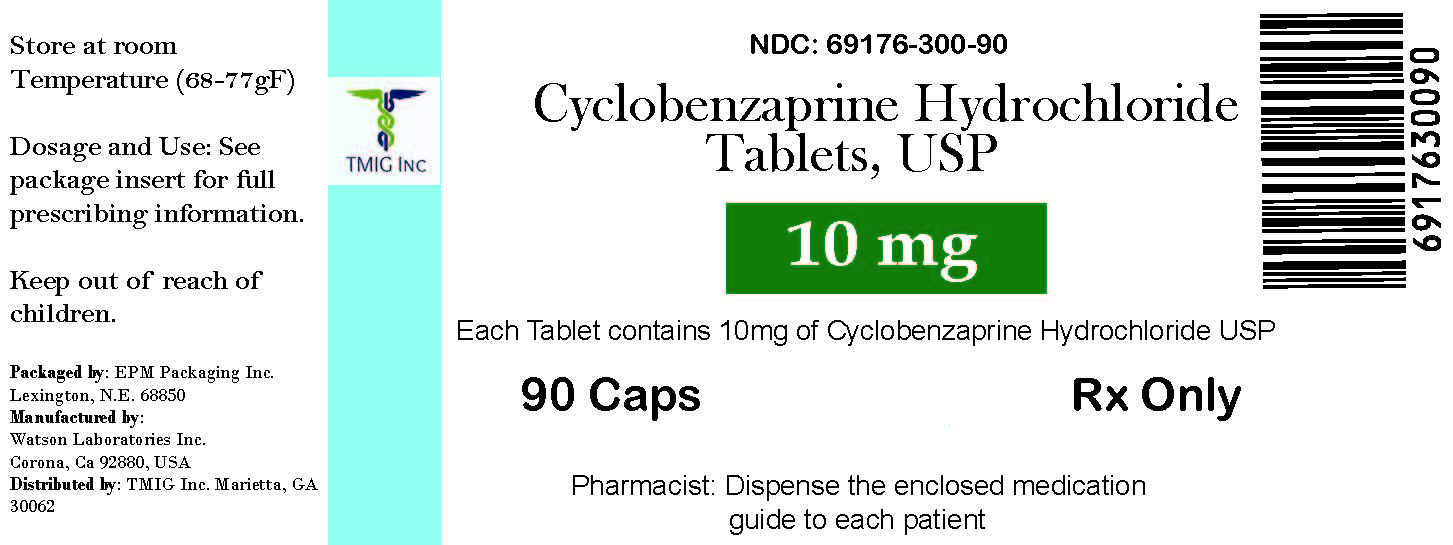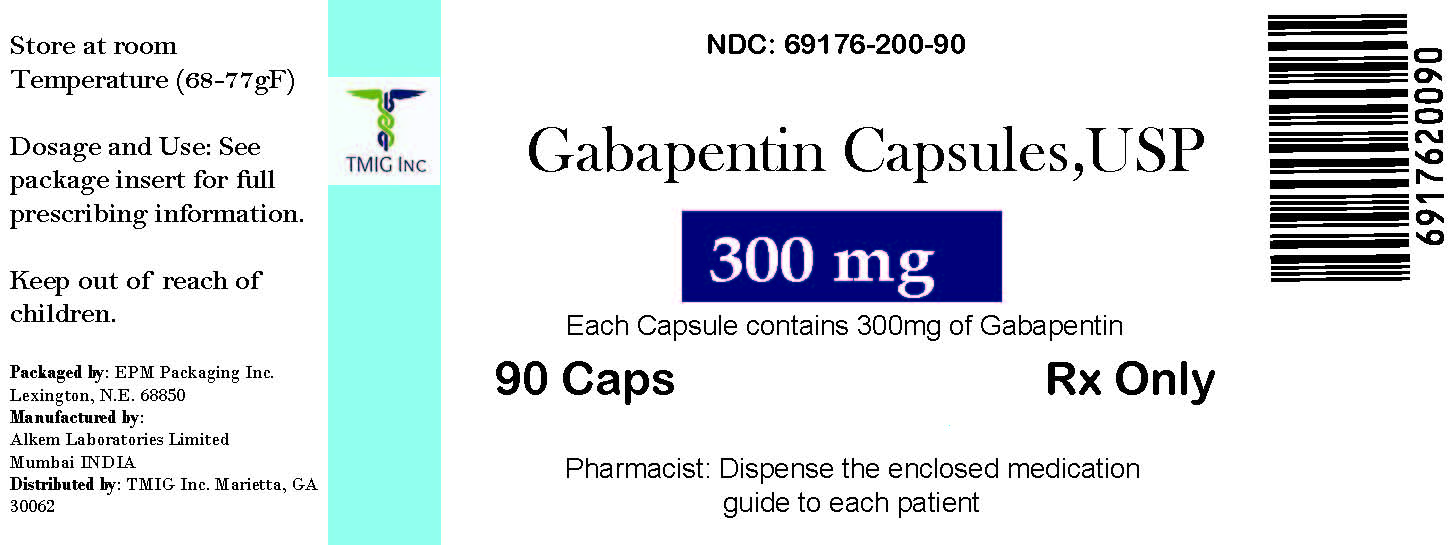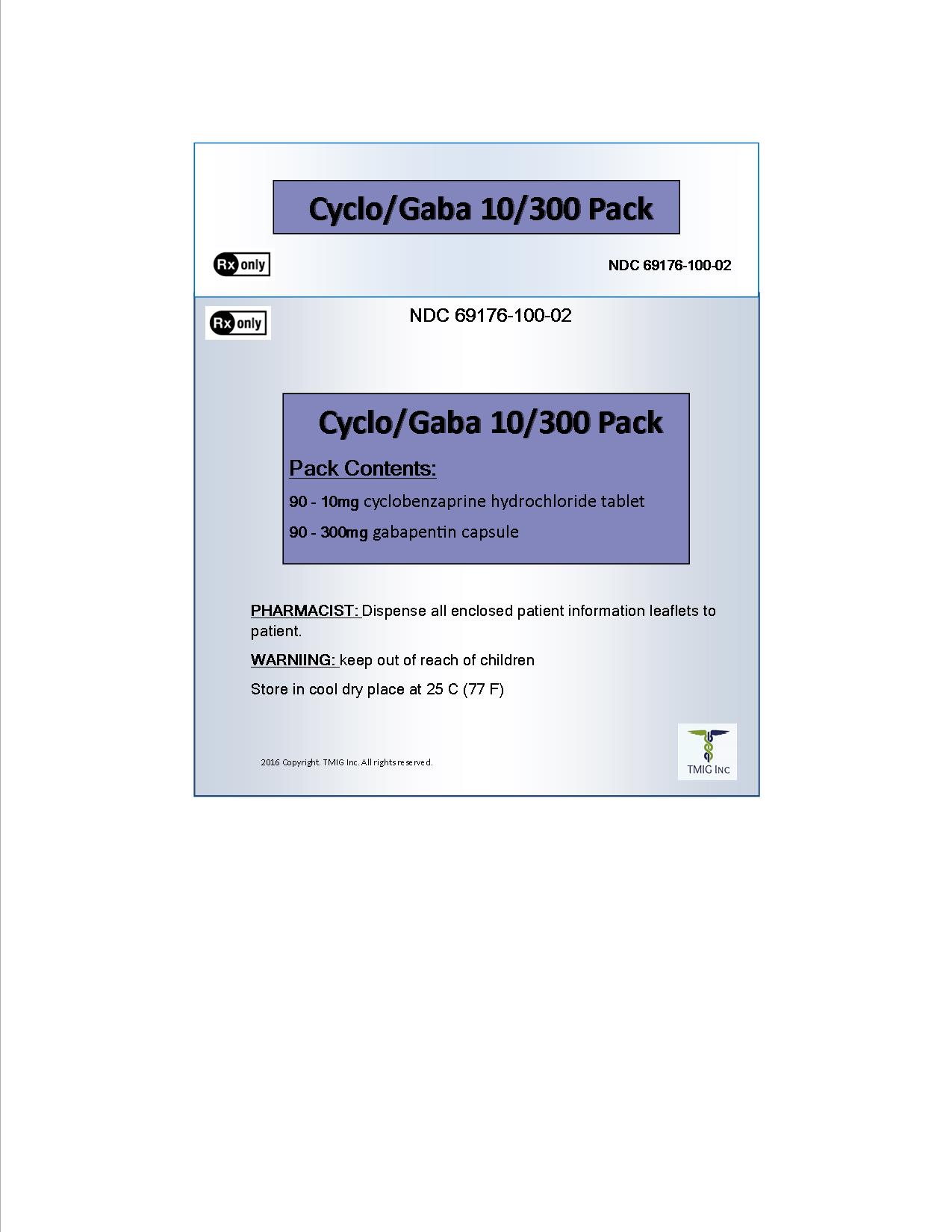 DRUG LABEL: Cyclo/Gaba 10/300 Pack
NDC: 69176-100 | Form: KIT | Route: ORAL
Manufacturer: TMIG Inc.
Category: prescription | Type: HUMAN PRESCRIPTION DRUG LABEL
Date: 20160622

ACTIVE INGREDIENTS: CYCLOBENZAPRINE HYDROCHLORIDE 10 mg/1 1; GABAPENTIN 300 mg/1 1
INACTIVE INGREDIENTS: SILICON DIOXIDE; CROSCARMELLOSE SODIUM; CALCIUM PHOSPHATE, DIBASIC, ANHYDROUS; CELLULOSE, MICROCRYSTALLINE; HYDROXYPROPYL CELLULOSE (TYPE H); HYPROMELLOSES; POLYETHYLENE GLYCOLS; MAGNESIUM STEARATE; TITANIUM DIOXIDE; STARCH, CORN; ANHYDROUS LACTOSE; TALC; GELATIN; SODIUM LAURYL SULFATE; FERRIC OXIDE YELLOW; TITANIUM DIOXIDE

Cyclo/Gaba 10/300 Pack

4 CONTRAINDICATIONS

Gabapentin is contraindicated in patients who havedemonstrated hypersensitivity to the drug or its ingredients.

7 DRUG INTERACTIONS

- Morphine increases gabapentin concentrations; dose adjustment may be needed (5.4, 7.2)

7.1 Other Antiepileptic Drugs

Gabapentin is not appreciably metabolized nor does it interfere with the metabolism of commonly coadministered antiepileptic drugs [see Clinical Pharmacology (12.3)] .

7.2 Opioids

Hydrocodone

Coadministration of gabapentin with hydrocodone decreases hydrocodone exposure [see Clinical Pharmacology (12.3)]. The potential for alteration in hydrocodone exposure and effect should be considered when gabapentin is started or discontinued in a patient taking hydrocodone.

Morphine

When gabapentin is administered with morphine, patients should be observed for signs of central nervous system (CNS) depression, such as somnolence, sedation and respiratory depression [see Clinical Pharmacology (12.3)] .

7.3 Maalox® (aluminum hydroxide, magnesium hydroxide)

The mean bioavailability of gabapentin was reduced by about 20% with concomitant use of an antacid (Maalox®) containing magnesium and aluminum hydroxides. It is recommended that gabapentin be taken at least 2 hours following Maalox administration [see Clinical Pharmacology (12.3)] .

7.4 Drug/Laboratory Test Interactions

Because false positive readings were reported withthe Ames N-Multistix SG® dipstick test for urinary protein whengabapentin was added to other antiepileptic drugs, the more specificsulfosalicylic acid precipitation procedure is recommended to determine thepresence of urine protein.

9 DRUG ABUSE AND DEPENDENCE

9.1 Controlled Substance

Gabapentin is not a scheduled drug.

9.2 Abuse

Gabapentin does not exhibit affinity for benzodiazepine, opiate (mu, delta or kappa), or cannabinoid 1 receptor sites. A small number of postmarketing cases report gabapentin misuse and abuse. These individuals were taking higher than recommended doses of gabapentin for unapproved uses. Most of the individuals described in these reports had a history of poly-substance abuse or used gabapentin to relieve symptoms of withdrawal from other substances. When prescribing gabapentin carefully evaluate patients for a history of drug abuse and observe them for signs and symptoms of gabapentin misuse or abuse (e.g. development of tolerance, self-dose escalation, and drug-seeking behavior).

9.3 Dependence

There are rare postmarketing reports of individuals experiencing withdrawal symptoms shortly after discontinuing higher than recommended doses of gabapentin used to treat illnesses for which the drug is not approved. Such symptoms included agitation, disorientation and confusion after suddenly discontinuing gabapentin that resolved after restarting gabapentin. Most of these individuals had a history of poly-substance abuse or used gabapentin to relieve symptoms of withdrawal from other substances. The dependence and abuse potential of gabapentin has not been evaluated in human studies.

10 OVERDOSAGE

A lethal dose of gabapentin was not identified in mice and rats receiving single oral doses as high as 8000 mg/kg. Signs of acute toxicity in animals included ataxia, labored breathing, ptosis, sedation, hypoactivity, or excitation.

Acute oral overdoses of gabapentin up to 49 grams have been reported. In these cases, double vision, slurred speech, drowsiness, lethargy, and diarrhea were observed. All patients recovered with supportive care. Coma, resolving with dialysis, has been reported in patients with chronic renal failure who were treated with gabapentin.

Gabapentin can be removed by hemodialysis. Although hemodialysis has not been performed in the few overdose cases reported, it may be indicated by the patients clinical state or in patients with significant renal impairment.

If overexposure occurs, call your poison control center at 1-800-222-1222.

12 CLINICAL PHARMACOLOGY

12.1 Mechanism of Action

The precise mechanisms by which gabapentin producesits analgesic and antiepileptic actions are unknown. Gabapentin is structurallyrelated to the neurotransmitter gamma-aminobutyric acid (GABA) but has noeffect on GABA binding, uptake, or degradation. In vitro studies haveshown that gabapentin binds with high-affinity to the α2δ subunit ofvoltage-activated calcium channels; however, the relationship of this bindingto the therapeutic effects of gabapentin is unknown.

16 HOW SUPPLIED/STORAGE AND HANDLING

Gabapentincapsules USP is supplied as follows:

100 mgcapsules:

White hardgelatin capsules imprinted “216” on body with blue ink, available in:

Bottles of 100:NDC 67877-222-01

Bottles of 500:NDC 67877-222-05

Bottles of1000: NDC 67877-222-10

300 mg capsules:

Yellow hardgelatin capsules imprinted “215” on body with blue ink, available in:

Bottles of 100:NDC 67877-223-01

Bottles of 500:NDC 67877-223-05

Bottles of1000: NDC 67877-223-10

400 mgcapsules:

Orange hardgelatin capsules imprinted “214” on body with blue ink, available in:

Bottles of 100:NDC 67877-224-01

Bottles of 500:NDC 67877-224-05

Bottles of1000: NDC 67877-224-10

Storage

Store at 20° to 25°C (68° to 77°F); [see USP Controlled Room Temperature].

17 PATIENT COUNSELING INFORMATION

Advise the patient to read the FDA-approved patient labeling (Medication Guide).

Drug Reaction with Eosinophilia and Systemic Symptoms (DRESS)/Multiorgan Hypersensitivity

Prior to initiation of treatment with gabapentin, instruct patients that a rash or other signs or symptoms of hypersensitivity (such as fever or lymphadenopathy) may herald a serious medical event and that the patient should report any such occurrence to a physician immediately [see Warnings and Precautions (5.1)] .

Anaphylaxis and Angioedema

Advise patients to discontinue gabapentin and seek medical care if they develop signs or symptoms of anaphylaxis or angioedema [ see Warnings and Precautions (5.2)].

Dizziness and Somnolence and Effects on Driving and Operating Heavy Machinery

Advise patients that gabapentin may cause dizziness, somnolence, and other symptoms and signs of CNS depression. Other drugs with sedative properties may increase these symptoms. Accordingly, although patients’ ability to determine their level of impairment can be unreliable, advise them neither to drive a car nor to operate other complex machinery until they have gained sufficient experience on gabapentin to gauge whether or not it affects their mental and/or motor performance adversely. Inform patients that it is not known how long this effect lasts [see Warnings and Precautions (5.3) and Warnings and Precautions (5.4)] .

Suicidal Thinking and Behavior

Counsel the patient, their caregivers, and families that AEDs, including gabapentin, may increase the risk of suicidal thoughts and behavior. Advise patients of the need to be alert for the emergence or worsening of symptoms of depression, any unusual changes in mood or behavior, or the emergence of suicidal thoughts, behavior, or thoughts about self-harm. Instruct patients to report behaviors of concern immediately to healthcare providers [see Warnings and Precautions (5.6)] .

Use in Pregnancy

Instruct patients to notify their physician if they become pregnant or intend to become pregnant during therapy, and to notify their physician if they are breast feeding or intend to breast feed during therapy [see Use in Specific Populations (8.1) and (8.3)] .

Encourage patients to enroll in the NAAED Pregnancy Registry if they become pregnant. This registry is collecting information about the safety of antiepileptic drugs during pregnancy. To enroll, patients can call the toll free number 1-888-233-2334 [see Use in Specific Populations (8.1)] .

This product’s label may have been updated. For full prescribing information, please visit www.dailymed.nlm.nih.gov.

Manufactured by:

Alkem Laboratories Limited

ALKEM HOUSE, Lower Parel,

Mumbai – 400 013, INDIA

Distributed by:

Ascend Laboratories, LCC

Montvale, NJ 07645
PT 1702-03

Medication Guide

Gabapentin Capsules USP

(GA ba PEN tin)

Read the Medication Guide before you start taking gabapentin and each time you get a refill. There may be new information. This information does not take the place of talking to your healthcare provider about your medical condition or treatment.

What is the most important information I should know about gabapentin?

Do not stop taking gabapentin without first talking to your healthcare provider.

Stopping gabapentin suddenly can cause serious problems.

Gabapentin can cause serious side effects including:

1. Suicidal Thoughts. Like other antiepileptic drugs, gabapentin may cause suicidal thoughts or actions in a very small number of people, about 1 in 500.

Call a healthcare provider right away if you have any of these symptoms, especially if they are new, worse, or worry you:

· thoughts about suicide or dying

· attempts to commit suicide

· new or worse depression

· new or worse anxiety

· feeling agitated or restless

· panic attacks

· trouble sleeping (insomnia)

· new or worse irritability

· acting aggressive, being angry, or violent

· acting on dangerous impulses

· an extreme increase in activity and talking (mania)

· other unusual changes in behavior or mood

How can I watch for early symptoms of suicidal thoughts and actions?

· Pay attention to any changes, especially sudden changes, in mood, behaviors, thoughts, or feelings.

· Keep all follow-up visits with your healthcare provider as scheduled.

Call your healthcare provider between visits as needed, especially if you are worried about symptoms.

Do not stop taking gabapentin without first talking to a healthcare provider.

· Stopping gabapentin suddenly can cause serious problems. Stopping a seizure medicine suddenly in a patient who has epilepsy can cause seizures that will not stop (status epilepticus).

· Suicidal thoughts or actions can be caused by things other than medicines. If you have suicidal thoughts or actions, your healthcare provider may check for other causes.

2. Changes in behavior and thinking -Using gabapentin in children 3 to 12 years of age can cause emotional changes, aggressive behavior, problems with concentration, restlessness, changes in school performance, and hyperactivity.

3. Gabapentin may cause a serious or life-threatening allergic reactions that may affect your skin or other parts of your body such as your liver or blood cells. This may cause you to be hospitalized or to stop gabapentin. You may or may not have a rash with an allergic reaction caused by gabapentin. Call a healthcare provider right away if you have any of the following symptoms:

· skin rash

· hives

· difficulty breathing

· fever

· swollen glands that do not go away

· swelling of your face, lips, throat, or tongue

· yellowing of your skin or of the whites of the eyes

· unusual bruising or bleeding

· severe fatigue or weakness

· unexpected muscle pain

· frequent infections

These symptoms may be the first signs of a serious reaction. A healthcare provider should examine you to decide if you should continue taking gabapentin.

What is gabapentin?

Gabapentin is a prescription medicine used to treat:

· Pain from damaged nerves (postherpetic pain) that follows healing of shingles (a painful rash that comes after a herpes zoster infection) in adults.

· Partial seizures when taken together with other medicines in adults and children 3 years of age and older with seizures.

Who should not take gabapentin?

Do not take gabapentin if you are allergic to gabapentin or any of the other ingredients in gabapentin. See the end of this Medication Guide for a complete list of ingredients in gabapentin.

What should I tell my healthcare provider before taking gabapentin?

Before taking gabapentin, tell your healthcare provider if you:

· have or have had kidney problems or are on hemodialysis

· have or have had depression, mood problems, or suicidal thoughts or behavior

· have diabetes

· are pregnant or plan to become pregnant. It is not known if gabapentin can harm your unborn baby. Tell your healthcare provider right away if you become pregnant while taking gabapentin. You and your healthcare provider will decide if you should take gabapentin while you are pregnant.

o If you become pregnant while taking gabapentin, talk to your healthcare provider about registering with the North American Antiepileptic Drug (NAAED) Pregnancy Registry. The purpose of this registry is to collect information about the safety of antiepileptic drugs during pregnancy. You can enroll in this registry by calling 1-888-233-2334.

· are breast-feeding or plan to breast-feed. Gabapentin can pass into breast milk. You and your healthcare provider should decide how you will feed your baby while you take gabapentin.

Tell your healthcare provider about all the medicines you take, including prescription and over-the-counter medicines, vitamins, and herbal supplements.

Taking gabapentin with certain other medicines can cause side effects or affect how well they work. Do not start or stop other medicines without talking to your healthcare provider.

Know the medicines you take. Keep a list of them and show it to your healthcare provider and pharmacist when you get a new medicine.

How should I take gabapentin?

· Take gabapentin exactly as prescribed. Your healthcare provider will tell you how much gabapentin to take.

o Do not change your dose of gabapentin without talking to your healthcare provider.

o Take gabapentin capsules with water.

If you take too much gabapentin, call your healthcare provider or your local Poison Control Center right away at 1-800-222-1222.

What should I avoid while taking gabapentin?

· Do not drink alcohol or take other medicines that make you sleepy or dizzy while taking gabapentin without first talking with your healthcare provider. Taking gabapentin with alcohol or drugs that cause sleepiness or dizziness may make your sleepiness or dizziness worse.

· Do not drive, operate heavy machinery, or do other dangerous activities until you know how gabapentin affects you. Gabapentin can slow your thinking and motor skills.

What are the possible side effects of gabapentin?

Gabapentin may cause serious side effects including:

See “What is the most important information I should know about gabapentin?”

· problems driving while using gabapentin. See “What I should avoid while taking gabapentin?”

· sleepiness and dizziness, which could increase the occurrence of accidental injury, including falls

· The most common side effects of gabapentin include:

· lack of coordination

· feeling tired

· viral infection

· fever

· feeling drowsy

· jerky movements

· nausea and vomiting

· difficulty with coordination

· difficulty with speaking

· double vision

· tremor

· unusual eye movement

· swelling, usually of legs and feet

Tell your healthcare provider if you have any side effect that bothers you or that does not go away.

These are not all the possible side effects of gabapentin. For more information, ask your healthcare provider or pharmacist.

Call your doctor for medical advice about side effects. You may report side effects to FDA at 1-800-FDA-1088.

How should I store gabapentin?

· Store gabapentin Capsules between 20° to 25°C (68° to 77°F); [see USP Controlled Room Temperature].

Keep gabapentin and all medicines out of the reach of children.

General information about the safe and effective use of gabapentin

Medicines are sometimes prescribed for purposes other than those listed in a Medication Guide. Do not use gabapentin for a condition for which it was not prescribed. Do not give gabapentin to other people, even if they have the same symptoms that you have. It may harm them.

This Medication Guide summarizes the most important information about gabapentin. If you would like more information, talk with your healthcare provider. You can ask your healthcare provider or pharmacist for information about gabapentin that was written for healthcare professionals.

What are the ingredients in gabapentin?

Active ingredient: gabapentin

Inactive ingredients in the capsules: anhydrous lactose, cornstarch, and talc. The 100-mg capsule shell also contains: gelatin, sodium lauryl sulfate, and titanium dioxide.

The 300-mg capsule shell also contains: gelatin, sodium lauryl sulfate, titanium dioxide, and yellow iron oxide.

The 400-mg capsule shell also contains: gelatin, sodium lauryl sulfate, red iron oxide, titanium dioxide, and yellow iron oxide. The imprinting ink contains shellac, dehydrated alcohol, isopropyl alcohol, butyl alcohol, propyl glycol, strong ammonia solution, and titanium dioxide.

Manufactured by:

Alkem Laboratories Limited

ALKEM HOUSE, Lower Parel,

Mumbai – 400 013, INDIA

Distributed by:

Ascend Laboratories, LCC.

Montvale, NJ 07645

Revised October 2015
PT 1702-03

Description

PACKAGE LABEL.PRINCIPAL DISPLAY PANEL

NDC 69176-200-90
GABAPENTIN CAPSULES, USP

300mg

PHARMACIST: Dispense the enclosed Medication Guide to each Patient.

Rx Only

90 Capsules

CYCLOBENZAPRINE TABLETS

10mg

PHARMACIST: Dispense the enclosed Medication Guide to each Patient.

Rx Only

90 Capsules